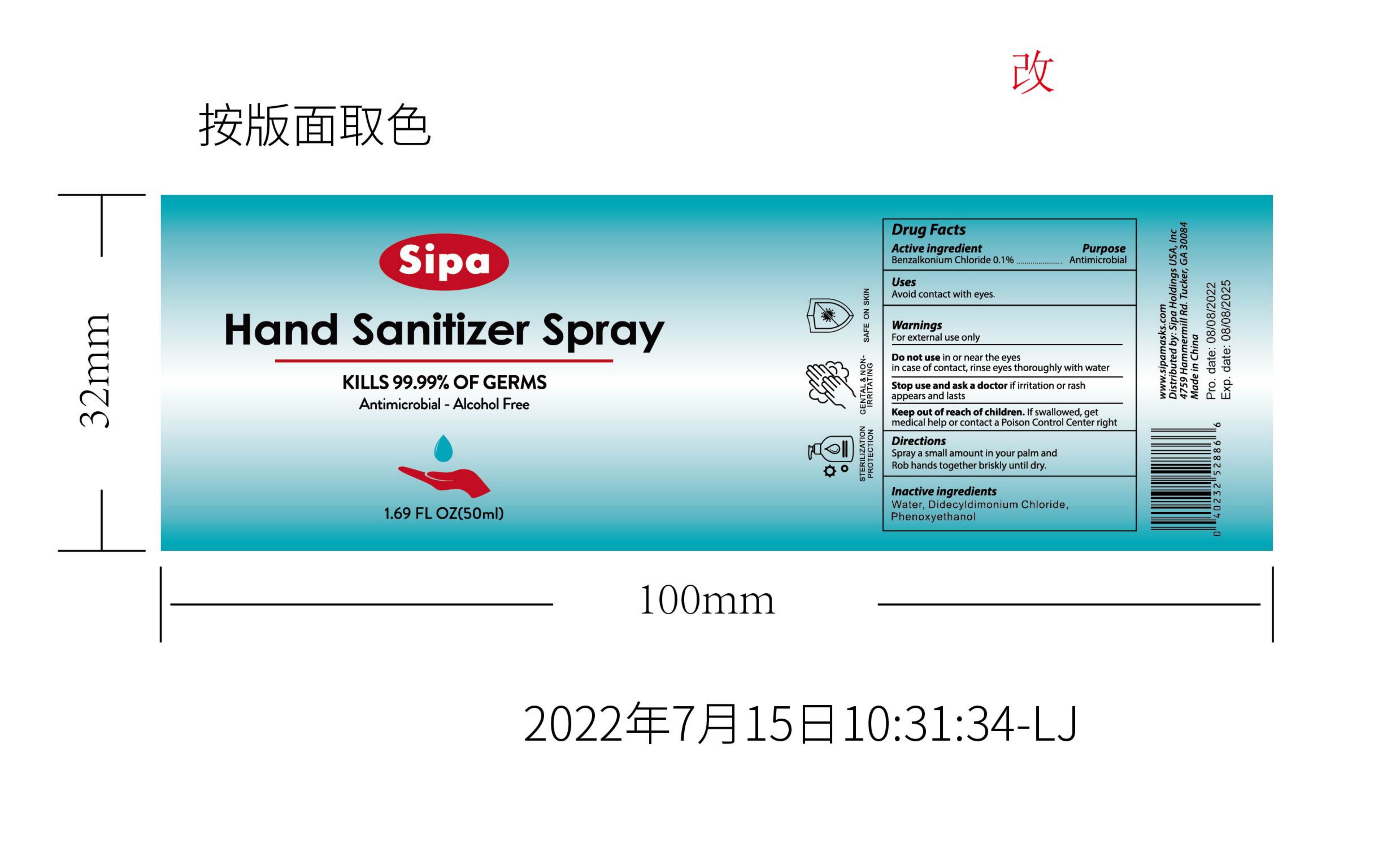 DRUG LABEL: Sipa hand sanitizer S.pray with Moisturizers
NDC: 83502-003 | Form: LIQUID
Manufacturer: Tourel (Changsha)Hotel Supplies Co.,Ltd
Category: otc | Type: HUMAN OTC DRUG LABEL
Date: 20250107

ACTIVE INGREDIENTS: BENZALKONIUM CHLORIDE 0.1 g/100 mL
INACTIVE INGREDIENTS: DIDECYLDIMONIUM CHLORIDE; PHENOXYETHANOL; WATER

83502-003 Update

Active Ingredient

Benzalkonium chloride 0.1%

Purpose

For hand sanitizing to decrease bacteria on the skin

Use

Avoid contact with eyes

Warnings

For external use only

Do not use in or near the eyes
in case of contact,rinse eyes thoroughly

When Using

Pay attention to the method of use. do not touch eyes

Stop Use

Stop use and ask a doctor if irritation or rash appears and lasts

Ask Doctor

if irritation or rashappears and lastsa

Keep Oot Of Reach Of Children

If swallowed, get medical help or contact a Poison Control Center right away

Directions

Spray a small amount in your palm and Rob hands together briskly until dry

Inactive ingredients

Water, Didecyldimonium Chloride, Phenoxvethanol